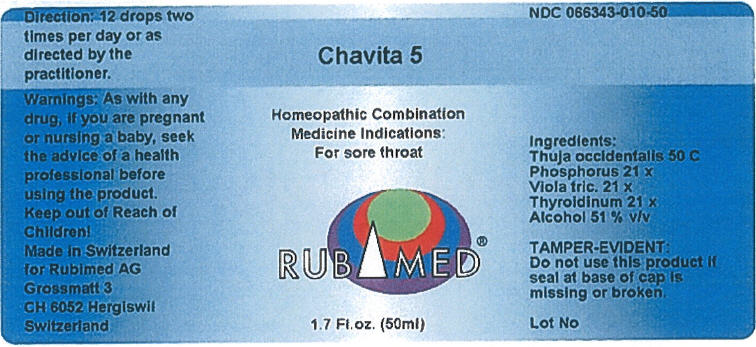 DRUG LABEL: Chavita 5
NDC: 66343-010 | Form: LIQUID
Manufacturer: RUBIMED AG
Category: otc | Type: HUMAN OTC DRUG LABEL
Date: 20150707

ACTIVE INGREDIENTS: THUJA OCCIDENTALIS LEAFY TWIG 50 [hp_C]/1 mL; PHOSPHORUS 21 [hp_X]/1 mL; VIOLA TRICOLOR 21 [hp_X]/1 mL; THYROID, PORCINE 21 [hp_X]/1 mL
INACTIVE INGREDIENTS: Alcohol 0.43 mL/1 mL

Chavita 5

PURPOSE

Homeopathic Combination Medicine Indications: For sore throat

ACTIVE INGREDIENT

INACTIVE INGREDIENT

Thuja occidentalis 50 C
Phosphorus 21 x
Viola tric. 21 x
Thyreoidinum 21 x
Alcohol 43 % v/v

TAMPER-EVIDENT

Do not use this product if seal at base of cap is missing or broken.

Direction

12 drops two times per day or as directed by the practitioner.

Warnings

PREGNANCY OR BREAST FEEDING

As with any drug, if you are pregnant or nursing a baby, seek the advice of a health professional before using the product.

Keep out of Reach of Children!

PRINCIPAL DISPLAY PANEL - 50 ml Bottle Label

Chavita 5

Homeopathic Combination
Medicine Indications:
For sore throat

RUBIMED®

1.7 Fl.oz. (50ml)